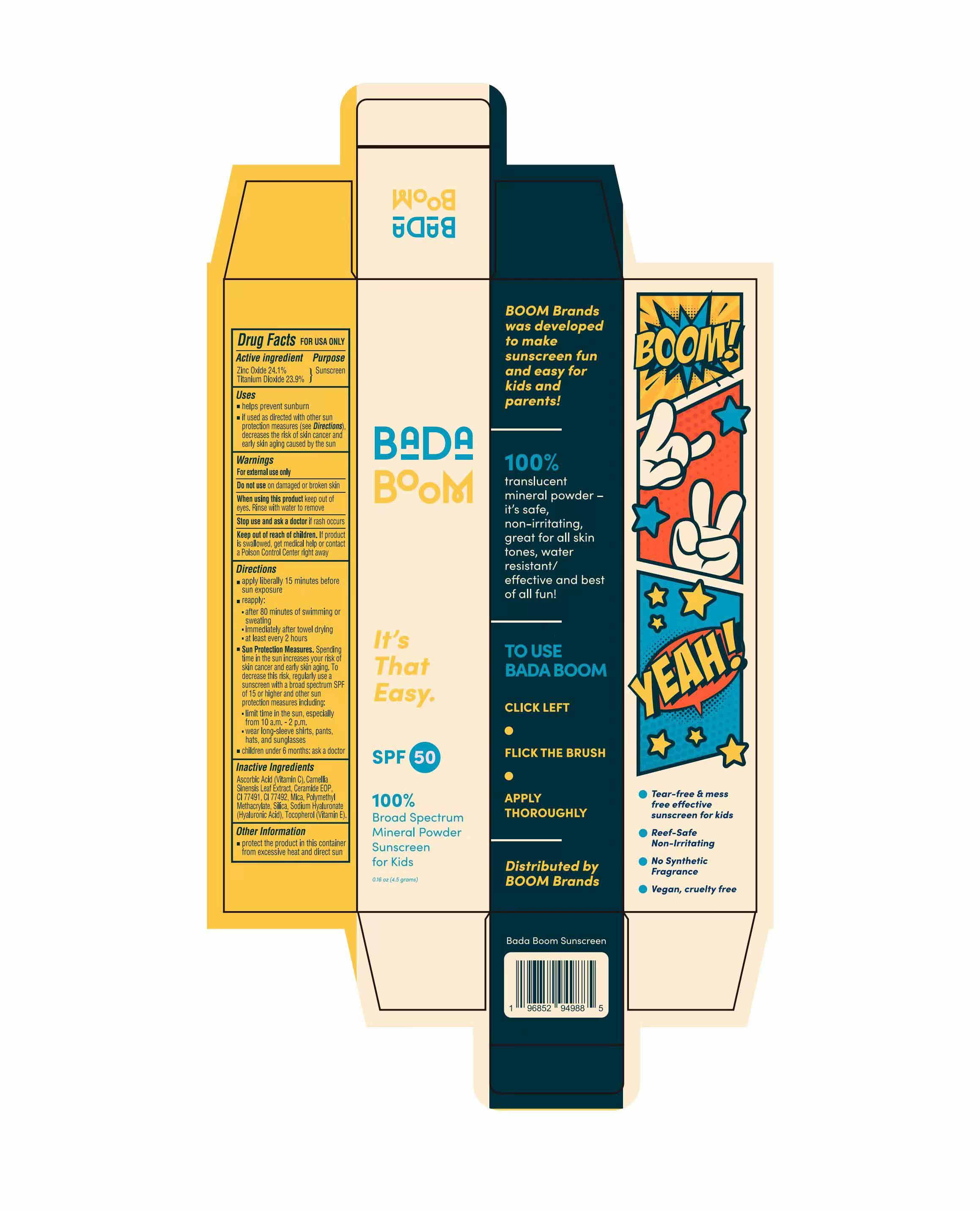 DRUG LABEL: BADABOOM SUNSCREEN
NDC: 87283-002 | Form: CREAM
Manufacturer: Aopline Biotechnology (Guangzhou) Co., Ltd.
Category: otc | Type: HUMAN OTC DRUG LABEL
Date: 20260108

ACTIVE INGREDIENTS: ZINC OXIDE 24.1 g/100 g; TITANIUM DIOXIDE 23.9 g/100 g
INACTIVE INGREDIENTS: .ALPHA.-TOCOPHEROL; CI 77492; POLY(METHYL METHACRYLATE; 450000 MW); HYALURONATE SODIUM; CERAMIDE 9; CI 77491; CAMELLIA SINENSIS LEAF; ASCORBIC ACID; MICA; SILICA

87283-002-01BadaBOOM Sunscreen

ACTIVE INGREDIENT

Zinc Oxide 24.1%
Titanium Dioxide 23.9%

PURPOSE

Sunscreen

Keep out of reach of children. If product is swallowed , get medical help or contact a Poison Control Center right away.

WARNINGS

For external use only.
Do not use on damaged or broken skin.
When using this product keep out of eyes. Rinse with water to remove.
Stop use and ask a doctor if rash occurs.
Keep out of reach of children. If product is swallowed , get medical help or contact a Poison Control Center right away.

DOSAGE AND ADMINISTRATION

apply liberally 15 minutes before sun exposure.
reapply :after 80 minutes of swimming or sweating.
immediately after towel drying.
at least every 2 hours.

INDICATIONS AND USAGE

apply liberally 15 minutes before sun exposure.
reapply :after 80 minutes of swimming or sweating.
immediately after towel drying.
at least every 2 hours.
Sun Protection Measures. Spending time in the sun increases your risk of skin cancer and early skin aging. To decrease this risk, regularly use a sunscreen with a broad spectrum SPF of 15 or higher and other sun protection measures including:
limit time in the sun, especially from 10 a m. -2 p.m.
wear long-sleeve shirts, pants, hats, and sunglasses.
children under 6 months: ask a doctor.

INACTIVE INGREDIENT

Ascorbic Acid (Vitamin C) , Camellia Sinensis Leaf Extract , Ceramide EOP, CI 77491 , CI 77492 , Mica , Polymethyl Methacrylate , Silica , Sodium Hyaluronate(Hyaluronic Acid) , Tocopherol (Vitamin E)